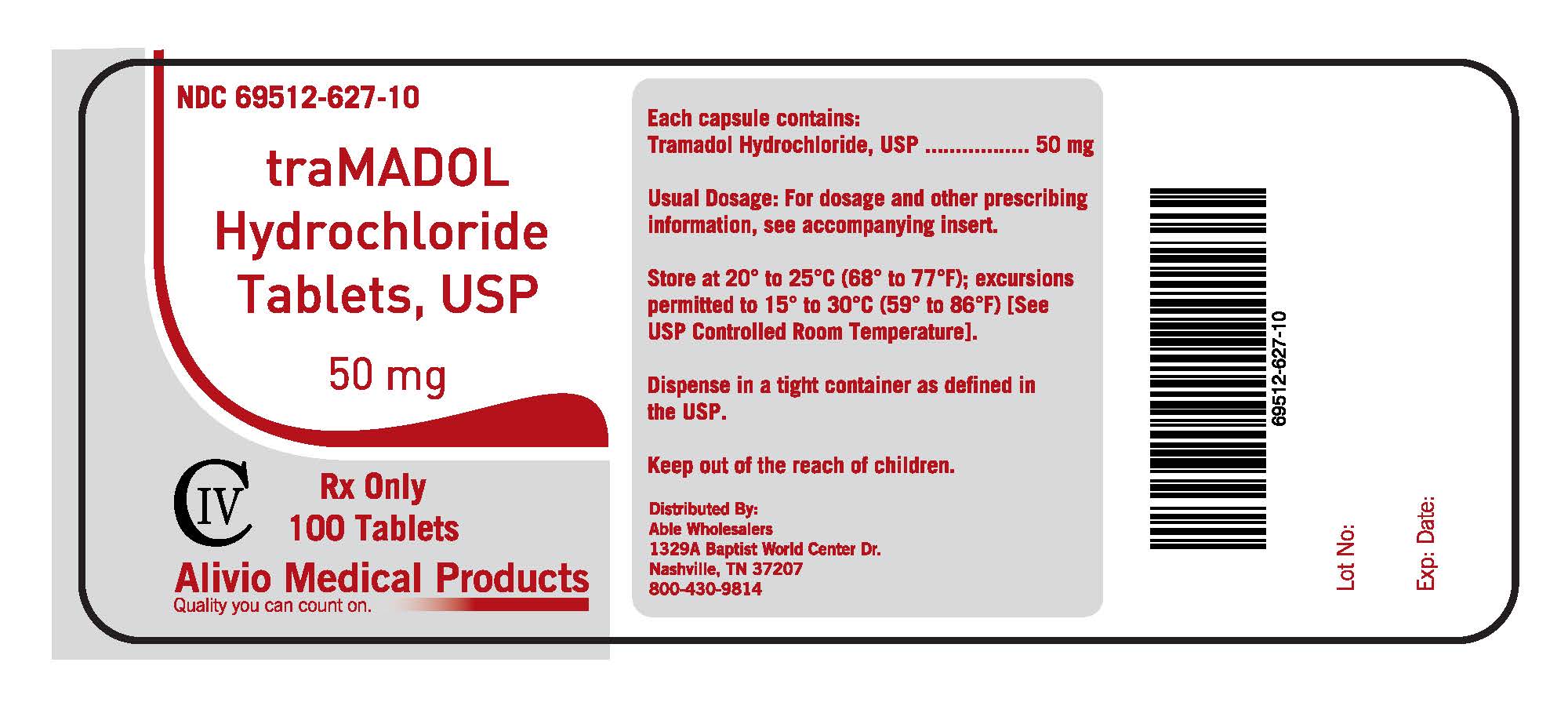 DRUG LABEL: TRAMADOL HYDROCHLORIDE 
NDC: 69512-627 | Form: TABLET
Manufacturer: Alivio Medical Products, LLC
Category: prescription | Type: HUMAN PRESCRIPTION DRUG LABEL
Date: 20151016

ACTIVE INGREDIENTS: TRAMADOL HYDROCHLORIDE 50 mg/50 mg
INACTIVE INGREDIENTS: LACTOSE MONOHYDRATE; SODIUM STARCH GLYCOLATE TYPE A POTATO; MAGNESIUM STEARATE; CELLULOSE, MICROCRYSTALLINE; POLYETHYLENE GLYCOLS; POLYSORBATE 80; TITANIUM DIOXIDE; HYPROMELLOSES; STARCH, CORN

Drug Facts

DESCRIPTION

Each capsule contains:

Tramadol Hydrochloride, USP ..........50 mg

DESCRIPTION

Usual Dosage: For dosage and other prescribing

information, see accompanying insert.

STORAGE AND HANDLING

Store at 20 to 25 C (68 to 77 F); excursions

permitted to 15 to 30 C (59 to 86 F)[See

USP Controlled Room Temperature]

Dispense in a tight container as defined in

the USP.

Keep out of reach of children.

DESCRIPTION

Tramadol hydrochloride tablets, USP are a centrally acting analgesic.

CLINICAL PHARMACOLOGY

PHARMACODYNAMICS Tramadol Hydrochloride contains tramadol, a centrally acting synthetic opoid

analgesic.

CLINICAL STUDIES

Tramadol hydrochloride has been given in single oral doses pf 50, 75 and 100 mg to patients with pain

following surgical procedures and pain following oral surgery (extraction if impacted molars).

INDICATIONS AND USAGE

Tramadol hydrochloride tablets, USP are indicated for the management of moderate to

moderately severe pain in adults.

CONTRAINDICATIONS

Tramadol hydrochloride tablets, USP should not be administered to patients who have previously

demonstrated hypersensitivity to tramadol, any other component of this product or opoids.

WARNINGS

Seizure Risk Seizures have been reported in patients receiving Tramadol hydrochloride within the

recommended dosage range.

PRECAUTIONS

Acute Abdominal Conditions The administration of tramadol hydrochloride may complicate the clinical assessment

of patients with acute abdominal conditions

ADVERSE REACTIONS

Tramadol hydrochloride was administered to 550 patients during the double-blind or open-label

extension periods in U.S. clinical studies of chronic nonmalignant pain.

DRUG ABUSE AND DEPENDENCE.

Abuse Tramadol has mu-opoid agonist activity.

OVERDOSAGE

Acute overdosage with tramadol can be manifested by respiratory depression, somnolence progressing to

stupor or coma, skeletal muscle flaccidity, cold and clammy skin, constricted pupils, seizures,

bradycardia, hypotension, cardiac arrest, and death.

DOSAGE AND ADMINISTRATION

Adults (17 years of age and older) For patients with moderate to moderately severe chronic pain not

requiringrapid onset of analgesic effect, the tolerability of tramadol hydrochloride, USP can be improved by

initiating therapy with a titration regimen: